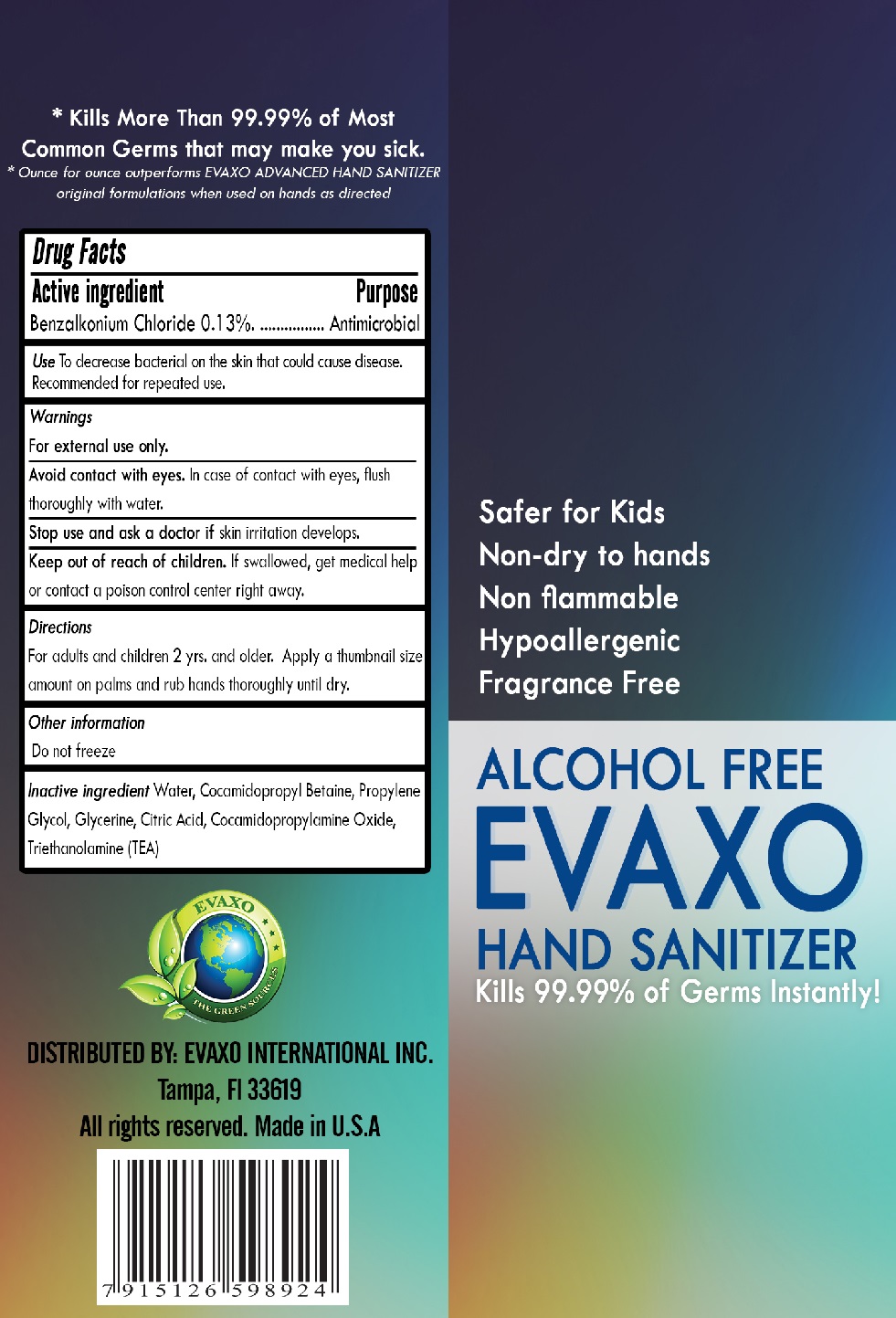 DRUG LABEL: EVAXO HAND SANITIZER
NDC: 78376-242 | Form: LIQUID
Manufacturer: Evaxo International Inc
Category: otc | Type: HUMAN OTC DRUG LABEL
Date: 20200604

ACTIVE INGREDIENTS: BENZALKONIUM CHLORIDE 1.3 mg/1 mL
INACTIVE INGREDIENTS: WATER; COCAMIDOPROPYL BETAINE; PROPYLENE GLYCOL; GLYCERIN; CITRIC ACID MONOHYDRATE; COCAMIDOPROPYLAMINE OXIDE; TROLAMINE

ALCOHOL FREE EVAXO HAND SANITIZER

Active ingredient

Benzalkonium Chloride 0.13%

Purpose

Antimicrobial

INDICATIONS AND USAGE

Use To decrease bacterial on the skin that could cause disease. Recommended for repeated use.

Warnings

For external use only.

Avoid contact with eyes. In case of contact with eyes, flush thoroughly with water.

Stop use and ask a doctor if skin irritation develops.

Keep out of reach of children. If swallowed, get medical help or contact poison control center right away.

Directions

For adults and children 2 yrs. and older. Apply a thumbnail size amount on palms and rub hands thoroughly until dry.

Other information

Do not freeze

Inactive ingredient Water, Cocamidopropyl Betaine, Propylene Glycol, Glycerine, Citric Acid, Cocamidopropylamine Oxide, Triethanolamine (TEA)

Safe for Kids

Non-dry to hands

Non flammable

Hypoallergenic

Fragrance Free

Kills 99.99% of Germs Instantly!

* Kills More Than 99.99% of Most Common Germs that may make you sick.

* Ounce for ounce outperforms EVAXO ADVANCED HAND SANITIZER original formulations when used on hands as directed

THE GREEN SOURCES

DISTRIBUTED BY: EVAXO INTERNATIONAL INC.

Tampa, FI 33619

All rights reserved. Made in U.S.A